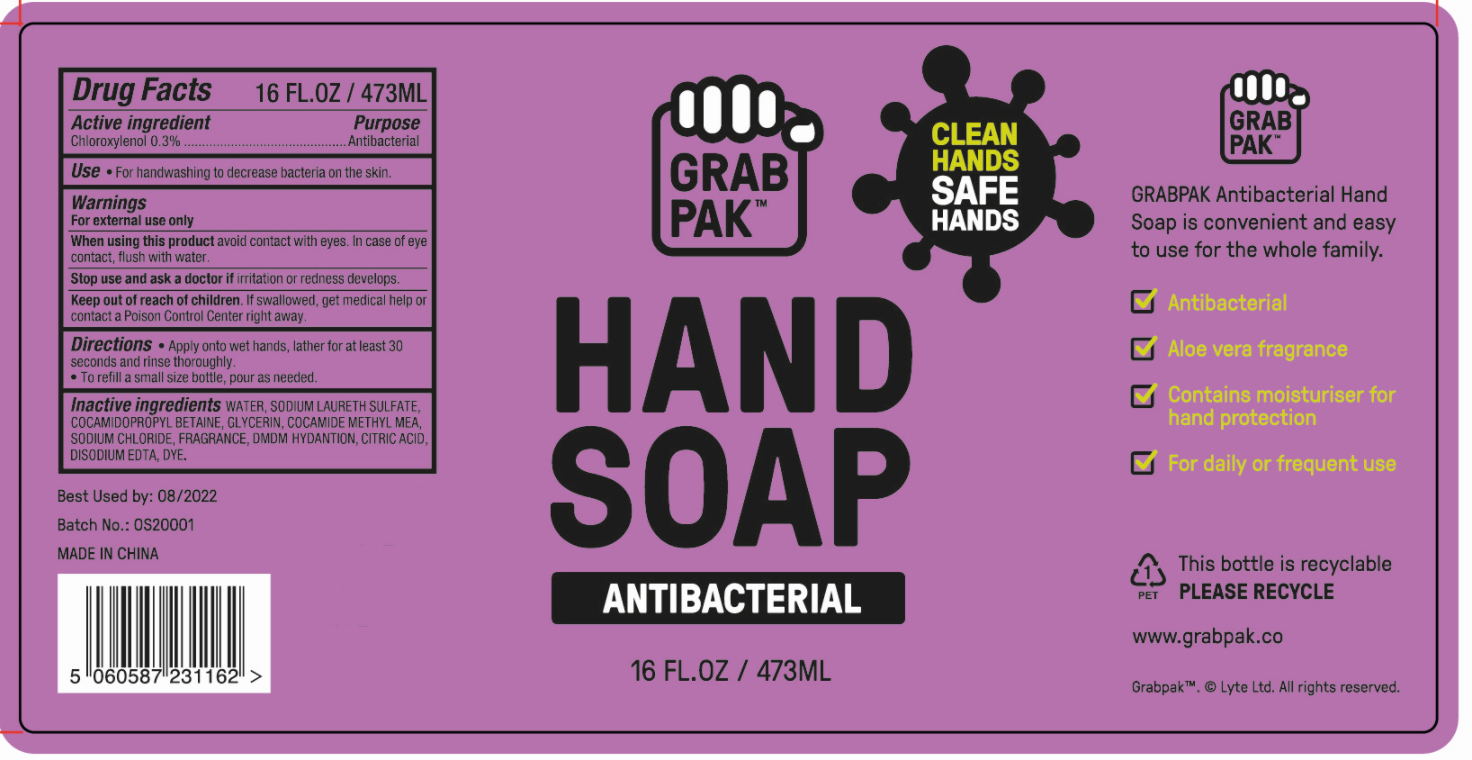 DRUG LABEL: HANDSOAP
NDC: 47993-317 | Form: LIQUID
Manufacturer: NINGBO JIANGBEI OCEAN STAR TRADING CO.,LTD
Category: otc | Type: HUMAN OTC DRUG LABEL
Date: 20201105

ACTIVE INGREDIENTS: CHLOROXYLENOL 0.3 g/100 mL
INACTIVE INGREDIENTS: WATER; SODIUM LAURETH SULFATE; COCAMIDOPROPYL BETAINE; GLYCERIN; COCOYL METHYL MONOETHANOLAMINE; SODIUM CHLORIDE; DMDM HYDANTOIN; ANHYDROUS CITRIC ACID; EDETATE DISODIUM

47993-317

Active ingredients

Chloroxylenol 0.3%

PURPOSE

Antibacterial

Uses：

For hanbwashing to decrease bacteria on the skin.

Warnings:

For external use only.

When using this product avoid contact with eyes. In case of eye contact, flush with water.

Stop use and ask a doctor if irritation or redness develops.

Keep out of reach of children. If swallowed，get medical help or contact a Poison Control Center right away.

Directions:

- Apply onto wet hands, lather for at least 30 second and rinse thoroughly.
- To refill a small size bottle, pour as needed.

Inactive Ingredients:

WATER, SODIUM LAURETH SULFATE, COCAMIDOPROPYL BETAINE, GLYCERIN, COCAMIDE METHYL MEA, SODIUM CHLORIDE, FRAGRANCE, DMDM HYDANTION, CITRIC ACID, DISODIUM EDTA, DYE.